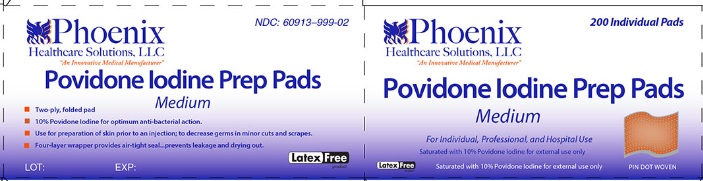 DRUG LABEL: Povidone Iodine Prep
NDC: 60913-999 | Form: SWAB
Manufacturer: PHOENIX HEALTHCARE SOLUTIONS, LLC
Category: otc | Type: HUMAN OTC DRUG LABEL
Date: 20251023

ACTIVE INGREDIENTS: POVIDONE-IODINE 1 g/100 mL
INACTIVE INGREDIENTS: CITRIC ACID MONOHYDRATE; GLYCERIN; WATER; SODIUM HYDROXIDE

Povidone Iodine Prep Pad

Active ingredient

Povidone Iodine USP 10% v/v

Purpose

Antiseptic

Uses

- Health-care antiseptic for preparation of the skin prior to surgery
- First aid antiseptic to help prevent the risk of skin infection in minor cuts, scrapes and burns

Warnings:

For external use only

Do not

- use in the eyes
- use on individuals who are allergic or sensitive to iodine
- apply over large areas of the body
- use as a first aid antiseptic longer than 1 week unless directed by a doctor.

Discontinue use if irritation and redness develop.

Consult a doctor in case of

- deep or puncture wounds
- animal bites
- serious burns

Stop use and consult a doctor

if the condition persists or gets worse.

Keep out of reach of children

If swallowed, get medical help or contact a Poison Control Center right away.

Directions:

For preparation of the skin prior to surgery

- clean the affected area
- apply a small amount of this product on the area

For use as a first aid antiseptic

- clean the affected area
- apply a small amount of this product on the area 1-3 times daily
- may be covered with a sterile bandage
- if bandaged, let dry first.

Other information

Store at room temperature: 59o - 86oF (15o - 30oC)

Inactive ingredients:

citric acid, glycerin, Makon 8, purified water, sodium hydroxide

Principal Display Panel

Phoenix Healthcare Solutions LLC

An Innovative Medical Manufacturer

NDC 60913-999-02

200 Individual Pads

Povidone Iodine Prep Pads

Medium

For Individual, Professional and Hospital Use

Saturated with 10% Povidone Iodine for external use only

Latex Free

PIN DOT WOVEN